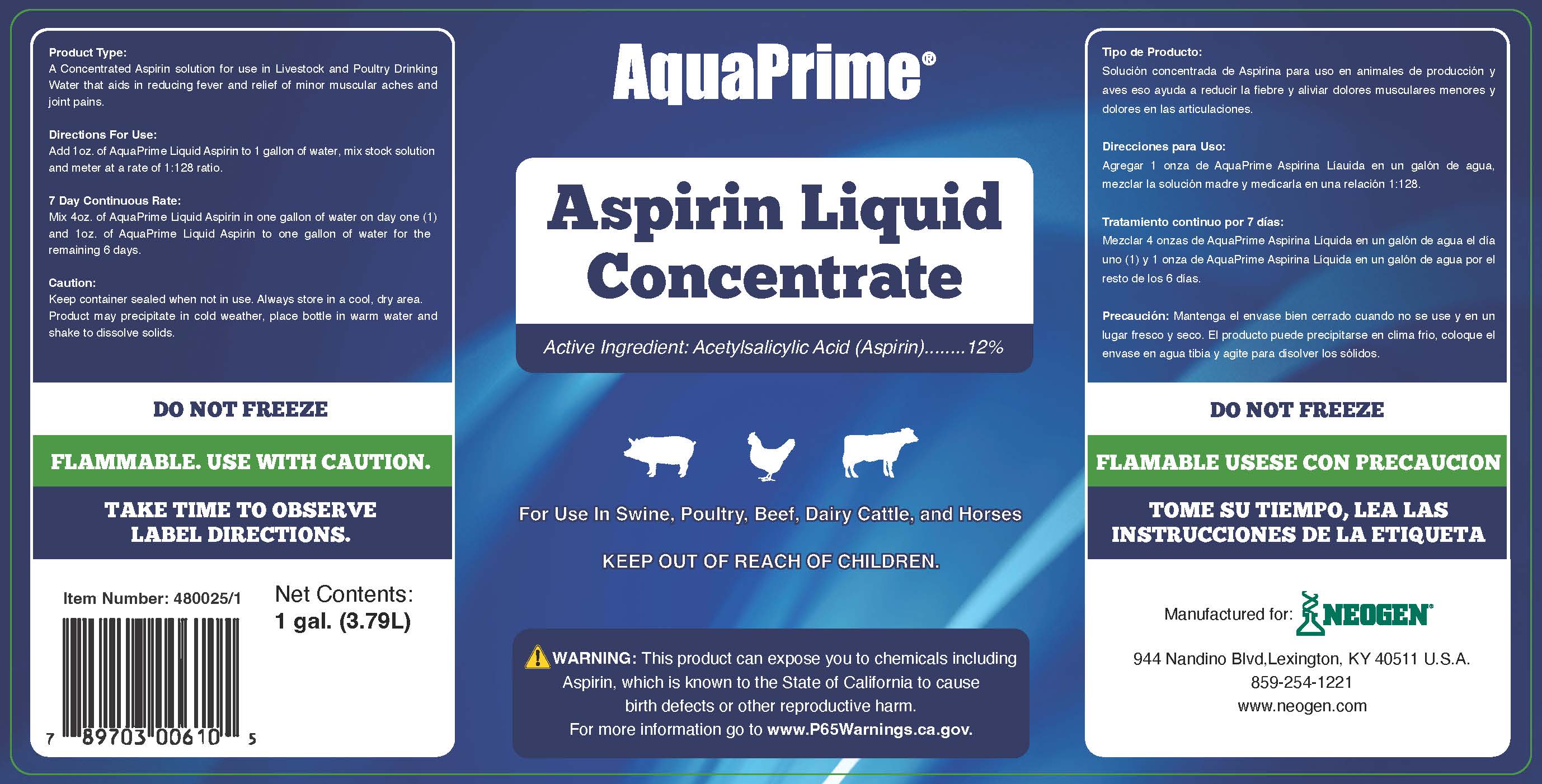 DRUG LABEL: AquaPrime Aspirin Liquid Concentrate
NDC: 86050-1120 | Form: LIQUID
Manufacturer: Blendpack, Inc.
Category: animal | Type: OTC ANIMAL DRUG LABEL
Date: 20230727

ACTIVE INGREDIENTS: ASPIRIN 120 g/1 L

AquaPrime Aspirin Liquid Concentrate

Product Type:

A concentrated Aspirin solution for use in Livestock and Poultry Drinking Water that aids in reducing fever and relief of minor muscular aches and joint pains.

Directions For Use:

Add 1 oz. of AquaPrime Liquid Aspirin to 1 gallon of water, mix stock solution and meter at a rate of 1:128 ratio.

7 Day Continuous Rate:

Mix 4 oz. of AquaPrime Liquid Aspirin in one gallon of water on day one (1) and 1 oz. of AquaPrime Liquid Aspirin to one gallon of water for the remaining 6 days.

Caution:

Keep container sealed when not in use. Always store in a cool, dry area.

Product may precipitate in cold weather, place bottle in warm water and shake to dissolve solids.

Do not freeze

Flammable. Use with Caution

Take time to observe label directions.

Keep out of reach of children.

PACKAGE LABEL

Add image transcription here...